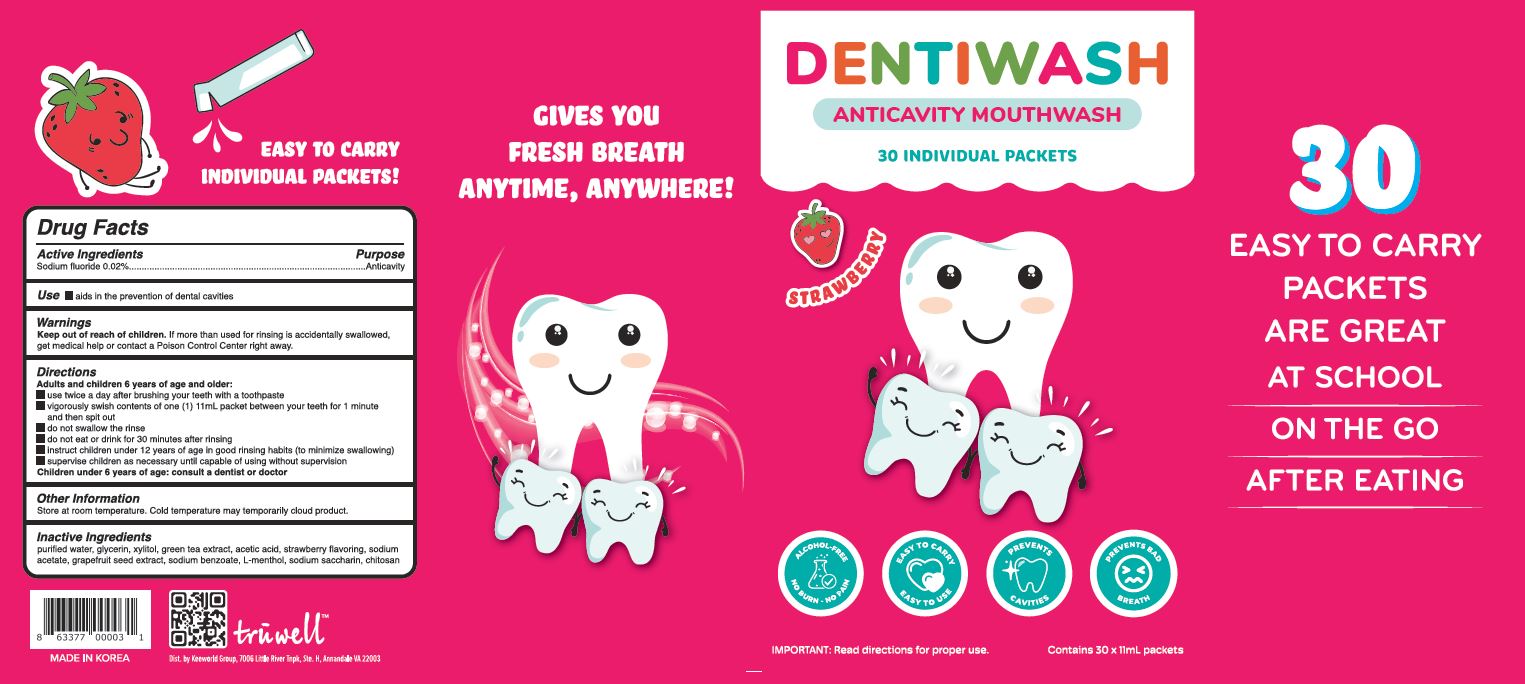 DRUG LABEL: Truwell Kids Dentiwash
NDC: 61284-0011 | Form: LIQUID
Manufacturer: ECOWORLDPHARM CO.,LTD
Category: otc | Type: HUMAN OTC DRUG LABEL
Date: 20231004

ACTIVE INGREDIENTS: SODIUM FLUORIDE 0.02 g/100 mL
INACTIVE INGREDIENTS: XYLITOL; GLYCERIN; WATER

Drug Facts

ACTIVE INGREDIENT

sodium fluoride

INACTIVE INGREDIENT

purified water, glycerin, xylitol, green tea extract, acetic acid, strawberry flavoring, sodium acetate, grapefruit seed extract, sodium benzoate, L-menthol, sodium saccharin, chitosan

PURPOSE

aids in the prevention of dental cavities

KEEP OUT OF REACH OF THE CHILDREN

INDICATIONS AND USAGE

Adults and children 6 years of age and older:

use twoce a day after brishing your teeth with a toothpaste

vigorously swish contents of one (1) 11mL packet between your teeth for 1 minute and then spit out

do not swallow the rinse

do not eat or drink for 30 minutes after rinsing

instruct children under 12 years of age in good rinsing habits (to minimize swallowing)

supervise children as necessary until capable of using without supervision

Children uder 6 years of age: consult a dentist or doctor

WARNINGS

if more than used for rinsing is accidentally swallowed, get medical help or contact a Poison Control Center right away

DOSAGE AND ADMINISTRATION

for dental use only